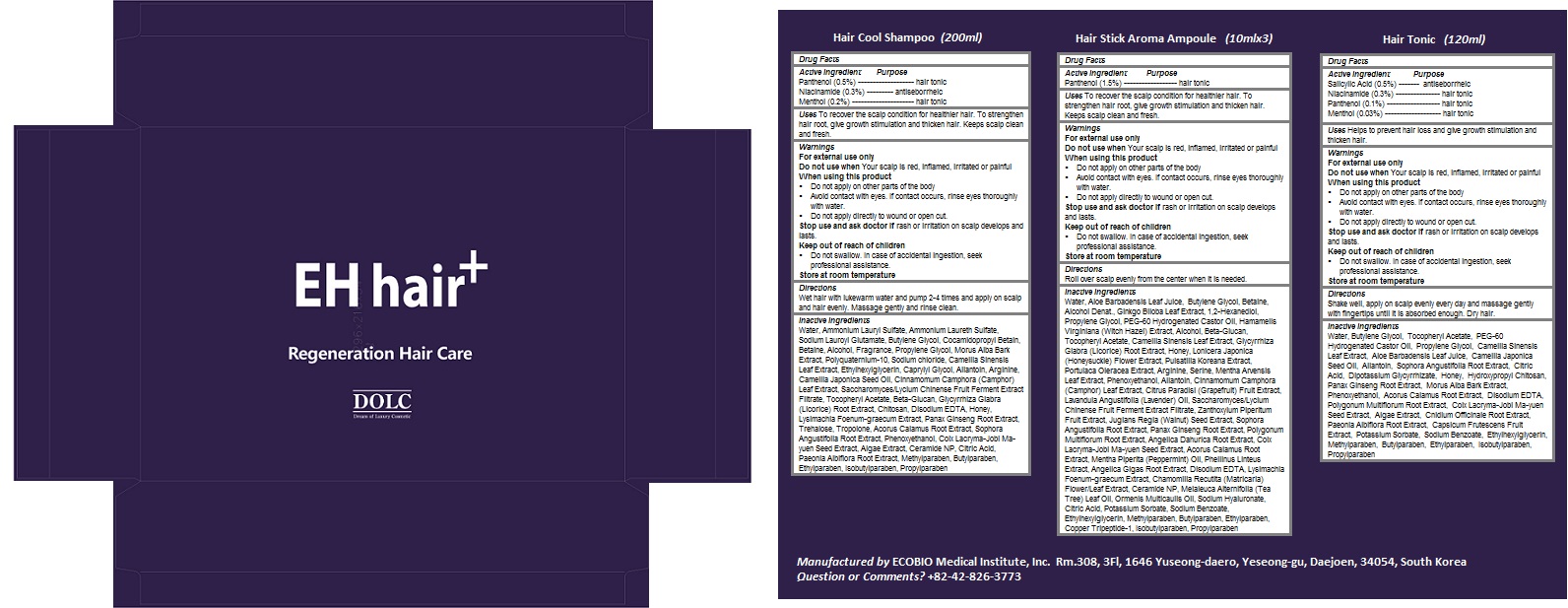 DRUG LABEL: EH Hair Plus Regeneration Hair Care
NDC: 70937-100 | Form: KIT | Route: TOPICAL
Manufacturer: ECOBIO Medical Institute, Inc.
Category: otc | Type: HUMAN OTC DRUG LABEL
Date: 20160829

ACTIVE INGREDIENTS: PANTHENOL 1 g/200 mL; NIACINAMIDE 0.6 g/200 mL; MENTHOL 0.4 g/200 mL; PANTHENOL 0.15 g/10 mL; SALICYLIC ACID 0.6 g/120 mL; NIACINAMIDE 0.36 g/120 mL; PANTHENOL 0.12 g/120 mL; MENTHOL 0.036 g/120 mL
INACTIVE INGREDIENTS: water; AMMONIUM LAURYL SULFATE; Sodium Lauroyl Glutamate; Butylene Glycol; COCAMIDOPROPYL BETAINE; Betaine; Alcohol; Propylene Glycol; MORUS ALBA BARK; POLYQUATERNIUM-10 (1000 MPA.S AT 2%); Sodium chloride; GREEN TEA LEAF; Ethylhexylglycerin; Caprylyl Glycol; Allantoin; Arginine; Camellia Japonica Seed Oil; CINNAMOMUM CAMPHORA LEAF; .ALPHA.-TOCOPHEROL ACETATE; GLYCYRRHIZA GLABRA; EDETATE DISODIUM ANHYDROUS; Honey; ASIAN GINSENG; Trehalose; Tropolone; ACORUS CALAMUS ROOT; SOPHORA FLAVESCENS ROOT; Phenoxyethanol; COIX LACRYMA-JOBI VAR. MA-YUEN SEED; Ceramide NP; CITRIC ACID MONOHYDRATE; PAEONIA LACTIFLORA ROOT; METHYLPARABEN; Butylparaben; Ethylparaben; Isobutylparaben; Propylparaben; WATER; ALOE VERA LEAF; Butylene Glycol; Betaine; ALCOHOL; GINKGO; 1,2-Hexanediol; Propylene Glycol; PEG-60 HYDROGENATED CASTOR OIL; HAMAMELIS VIRGINIANA TOP; .ALPHA.-TOCOPHEROL ACETATE; GREEN TEA LEAF; Honey; LONICERA JAPONICA FLOWER; PULSATILLA KOREANA ROOT; PURSLANE; Arginine; MENTHA ARVENSIS LEAF; Phenoxyethanol; Allantoin; CINNAMOMUM CAMPHORA LEAF; GRAPEFRUIT; LAVENDER OIL; ZANTHOXYLUM PIPERITUM FRUIT PULP; ENGLISH WALNUT; SOPHORA FLAVESCENS ROOT; ASIAN GINSENG; FALLOPIA MULTIFLORA ROOT; ANGELICA DAHURICA ROOT; COIX LACRYMA-JOBI VAR. MA-YUEN SEED; ACORUS CALAMUS ROOT; PEPPERMINT OIL; ANGELICA GIGAS ROOT; EDETATE DISODIUM ANHYDROUS; MATRICARIA RECUTITA FLOWERING TOP; Ceramide NP; TEA TREE OIL; CLADANTHUS MIXTUS WHOLE; HYALURONATE SODIUM; CITRIC ACID MONOHYDRATE; Potassium Sorbate; SODIUM BENZOATE; ETHYLHEXYLGLYCERIN; Methylparaben; Butylparaben; Ethylparaben; PREZATIDE COPPER; Isobutylparaben; Propylparaben; WATER; Butylene Glycol; .ALPHA.-TOCOPHEROL ACETATE; PEG-60 HYDROGENATED CASTOR OIL; Propylene Glycol; GREEN TEA LEAF; ALOE VERA LEAF; CAMELLIA JAPONICA SEED OIL; Allantoin; SOPHORA FLAVESCENS ROOT; CITRIC ACID MONOHYDRATE; GLYCYRRHIZINATE DIPOTASSIUM; Honey; ASIAN GINSENG; MORUS ALBA BARK; Phenoxyethanol; ACORUS CALAMUS ROOT; EDETATE DISODIUM ANHYDROUS; FALLOPIA MULTIFLORA ROOT; COIX LACRYMA-JOBI VAR. MA-YUEN SEED; CNIDIUM OFFICINALE ROOT; PAEONIA LACTIFLORA ROOT; TABASCO PEPPER; POTASSIUM SORBATE; Sodium Benzoate; Ethylhexylglycerin; Methylparaben; Butylparaben; Ethylparaben; Isobutylparaben; Propylparaben

EH Hair Plus Regeneration Hair Care

Active Ingredients

Hair cool shampoo

- Panthenol (0.5%)

- Niacinamide (0.3%)

- Menthol (0.2%)

Hair stick aroma ampoule

- Panthenol (1.5%)

Hair tonic

- Salicylic Acid (0.5%)

- Niacinamide (0.3%)

- Panthenol (0.1%)

- Menthol (0.03%)

Purpose

- hair tonic

- antiseborrheic

Keep out of reach of children

- Do not swallow. In case of accidental ingestion, seek professional assistance.

Uses

Hair cool shampoo

- To recover the scalp condition for healthier hair. To strengthen hair root, give growth stimulation and thicken hair. Keeps scalp clean and fresh.

Hair stick aroma ampoule

- To recover the scalp condition for healthier hair. To strengthen hair root, give growth stimulation and thicken hair. Keeps scalp clean and fresh.

Hair tonic

- Helps to prevent hair loss and give growth stimulation and thicken hair.

Warnings

For external use only
Do not use when Your scalp is red, inflamed, irritated or painful
When using this product
- Do not apply on other parts of the body
- Avoid contact with eyes. If contact occurs, rinse eyes thoroughly with water.
- Do not apply directly to wound or open cut.
Stop use and ask doctor if rash or irritation on scalp develops and lasts.

Store at room temperature

Directions

Hair cool shampoo

- Wet hair with lukewarm water and pump 2-4 times and apply on scalp and hair evenly. Massage gently and rinse clean.

Hair stick aroma ampoule

- Roll over scalp evenly from the center when it is needed.

Hair tonic

- Shake well, apply on scalp evenly every day and massage gently with fingertips until it is absorbed enough. Dry hair.

Inactive Ingredients

Hair cool shampoo

- Water, Ammonium Lauryl Sulfate, Ammonium Laureth Sulfate, Sodium Lauroyl Glutamate, Butylene Glycol, Cocamidopropyl Betain, Betaine, Alcohol, Fragrance, Propylene Glycol, Morus Alba Bark Extract, Polyquaternium-10, Sodium chloride, Camellia Sinensis Leaf Extract, Ethylhexylglycerin, Caprylyl Glycol, Allantoin, Arginine, Camellia Japonica Seed Oil, Cinnamomum Camphora (Camphor) Leaf Extract, Saccharomyces/Lycium Chinense Fruit Ferment Extract Filtrate, Tocopheryl Acetate, Beta-Glucan, Glycyrrhiza Glabra (Licorice) Root Extract, Chitosan, Disodium EDTA, Honey, Lysimachia Foenum-graecum Extract, Panax Ginseng Root Extract, Trehalose, Tropolone, Acorus Calamus Root Extract, Sophora Angustifolia Root Extract, Phenoxyethanol, Coix Lacryma-Jobi Ma-yuen Seed Extract, Algae Extract, Ceramide NP, Citric Acid, Paeonia Albiflora Root Extract, Methylparaben, Butylparaben, Ethylparaben, Isobutylparaben, Propylparaben

Hair stick aroma ampoule

- Water, Aloe Barbadensis Leaf Juice, Butylene Glycol, Betaine, Alcohol Denat., Ginkgo Biloba Leaf Extract, 1,2-Hexanediol, Propylene Glycol, PEG-60 Hydrogenated Castor Oil, Hamamelis Virginiana (Witch Hazel) Extract, Alcohol, Beta-Glucan, Tocopheryl Acetate, Camellia Sinensis Leaf Extract, Glycyrrhiza Glabra (Licorice) Root Extract, Honey, Lonicera Japonica (Honeysuckle) Flower Extract, Pulsatilla Koreana Extract, Portulaca Oleracea Extract, Arginine, Serine, Mentha Arvensis Leaf Extract, Phenoxyethanol, Allantoin, Cinnamomum Camphora (Camphor) Leaf Extract, Citrus Paradisi (Grapefruit) Fruit Extract, Lavandula Angustifolia (Lavender) Oil, Saccharomyces/Lycium Chinense Fruit Ferment Extract Filtrate, Zanthoxylum Piperitum Fruit Extract, Juglans Regia (Walnut) Seed Extract, Sophora Angustifolia Root Extract, Panax Ginseng Root Extract, Polygonum Multiflorum Root Extract, Angelica Dahurica Root Extract, Coix Lacryma-Jobi Ma-yuen Seed Extract, Acorus Calamus Root Extract, Mentha Piperita (Peppermint) Oil, Phellinus Linteus Extract, Angelica Gigas Root Extract, Disodium EDTA, Lysimachia Foenum-graecum Extract, Chamomilla Recutita (Matricaria) Flower/Leaf Extract, Ceramide NP, Melaleuca Alternifolia (Tea Tree) Leaf Oil, Ormenis Multicaulis Oil, Sodium Hyaluronate, Citric Acid, Potassium Sorbate, Sodium Benzoate, Ethylhexylglycerin, Methylparaben, Butylparaben, Ethylparaben, Copper Tripeptide-1, Isobutylparaben, Propylparaben

Hair tonic

- Water, Butylene Glycol, Tocopheryl Acetate, PEG-60 Hydrogenated Castor Oil, Propylene Glycol, Camellia Sinensis Leaf Extract, Aloe Barbadensis Leaf Juice, Camellia Japonica Seed Oil, Allantoin, Sophora Angustifolia Root Extract, Citric Acid, Dipotassium Glycyrrhizate, Honey, Hydroxypropyl Chitosan, Panax Ginseng Root Extract, Morus Alba Bark Extract, Phenoxyethanol, Acorus Calamus Root Extract, Disodium EDTA, Polygonum Multiflorum Root Extract, Coix Lacryma-Jobi Ma-yuen Seed Extract, Algae Extract, Cnidium Officinale Root Extract, Paeonia Albiflora Root Extract, Capsicum Frutescens Fruit Extract, Potassium Sorbate, Sodium Benzoate, Ethylhexylglycerin, Methylparaben, Butylparaben, Ethylparaben, Isobutylparaben, Propylparaben